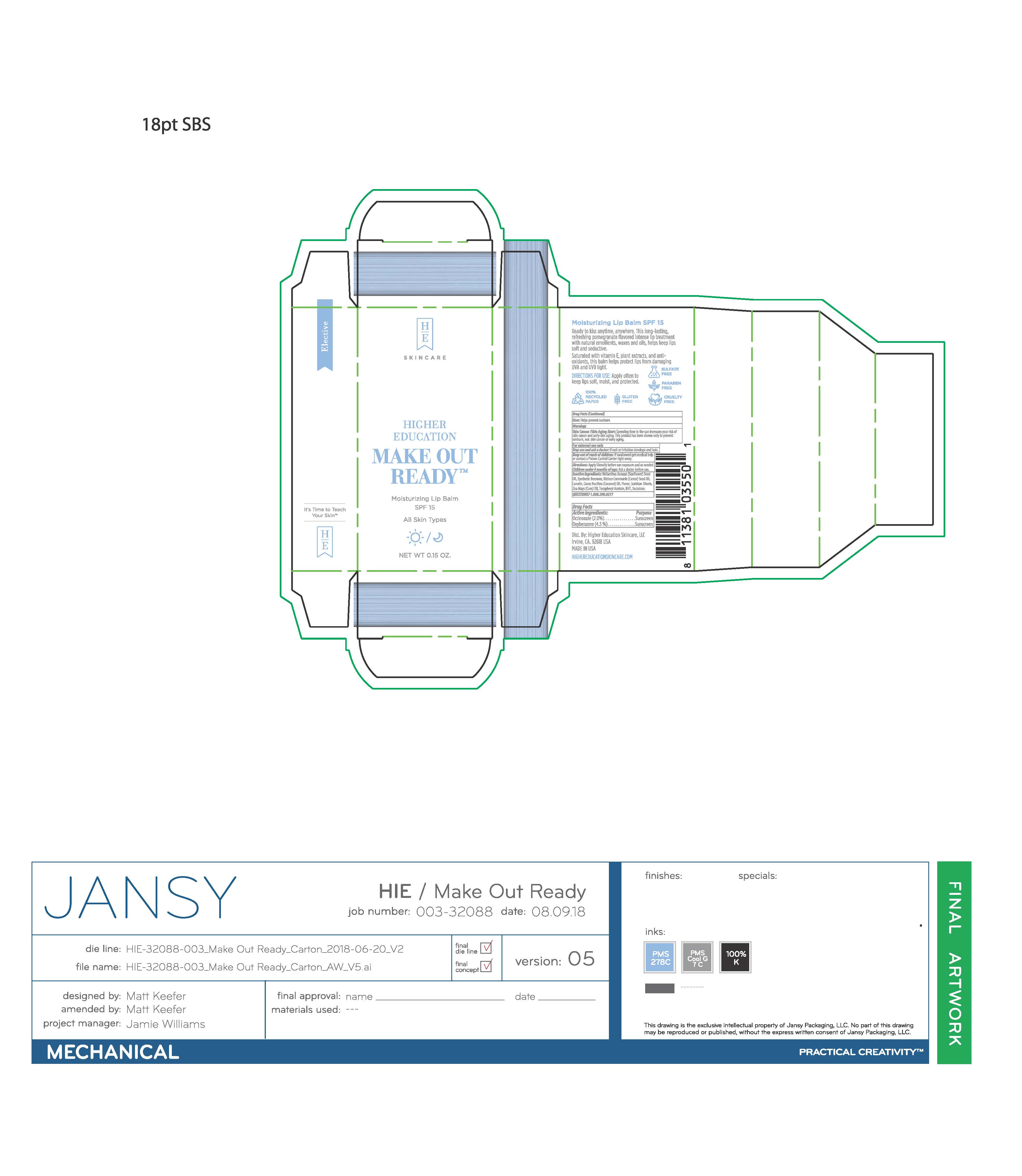 DRUG LABEL: Higher Education Make Out Ready Moisturizing Lip Balm SPF 15
NDC: 72936-020 | Form: LIPSTICK
Manufacturer: Higher Education Skincare, LLC
Category: otc | Type: HUMAN OTC DRUG LABEL
Date: 20210111

ACTIVE INGREDIENTS: OCTINOXATE 2 g/100 g; OXYBENZONE 4.5 g/100 g
INACTIVE INGREDIENTS: HELIANTHUS ANNUUS SEED WAX; SYNTHETIC WAX (1200 MW); CASTOR OIL; LANOLIN; COCONUT OIL; SORBITAN MONOOLEATE; CORN OIL; .ALPHA.-TOCOPHEROL ACETATE; SUCRALOSE

DRUG FACTS

Active Ingredients

Octinoxate 2.0%

Oxybenzone 4.5%

Uses

• helps prevent sunburn

Warnings

For external use only
Do not use on damaged or broken skin
Skin Cancer/Skin Aging Alert: Spending time in the sun increases your risk of skin cancer and early skin aging. This product has been shown only to prevent sunburn, not skin cancer or early aging.
Stop use and ask a docor if rash or irritation develops and lasts
Keep out of reach of children. If swalled, get medical help or contact a Poison Control Center right away.

Directions

• apply liberally before sun exposure and as needed.
• children under 6 months of age: Ask a doctor

Inactive ingredients

Helianthus Annuus (Sunflower) Seed Oil, Synthetic Beeswax, Ricinus Communis (Castor) Seed Oil, Lanolin, Cocos Nucifera (Coconut) Oil, Aroma/Flavor, Sorbitan Oleate, Zea Mays (Corn) Oil, Tocopheryl Acetate, BHT, Sucralose

Questions or Comments?

1.800.290.0577